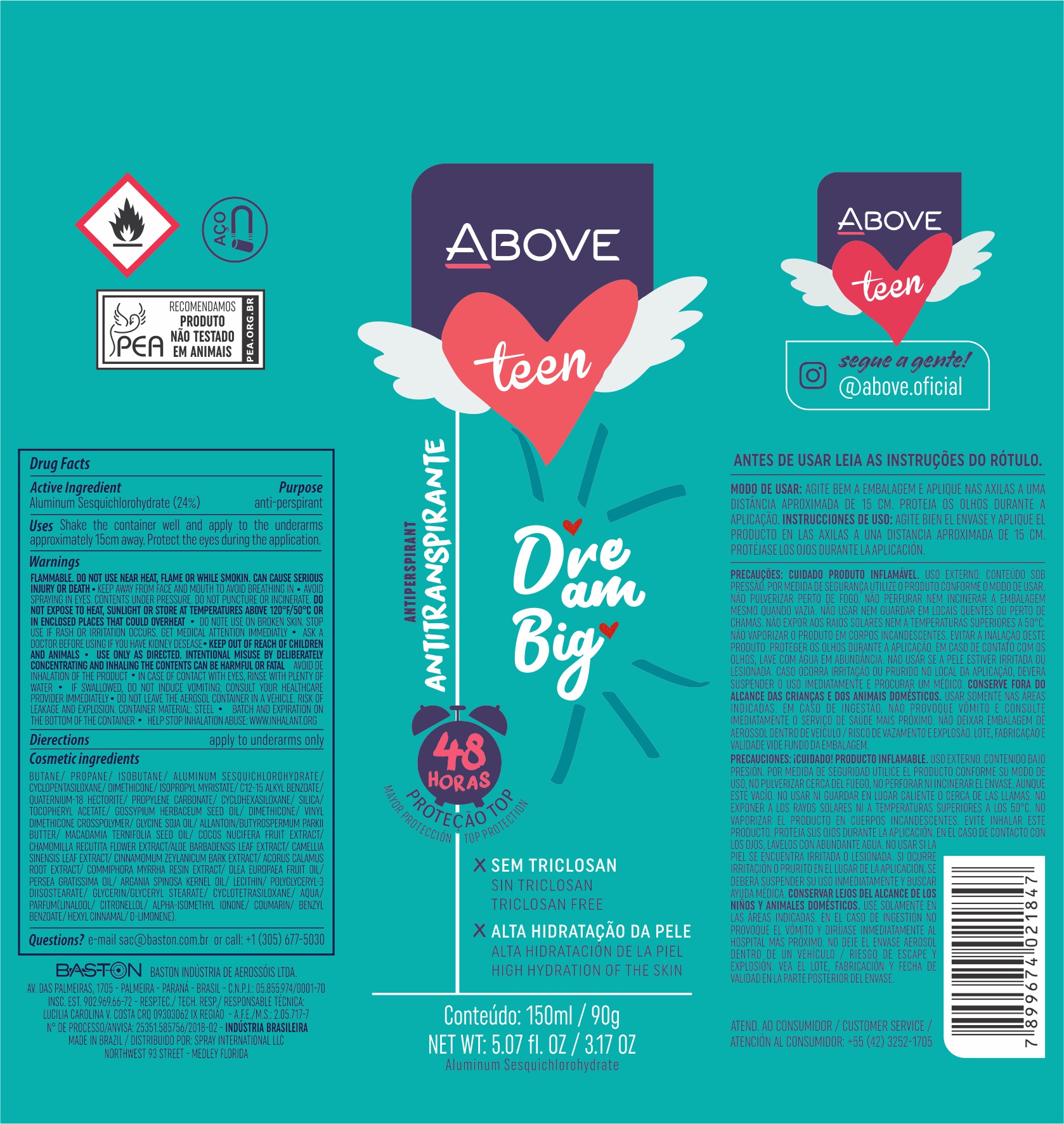 DRUG LABEL: Antiperspirant Above Teen Dream Big
NDC: 73306-1110 | Form: AEROSOL, SPRAY
Manufacturer: Baston Industria de Aerossóis Ltda
Category: otc | Type: HUMAN OTC DRUG LABEL
Date: 20241226

ACTIVE INGREDIENTS: ALUMINUM SESQUICHLOROHYDRATE 24 g/100 g
INACTIVE INGREDIENTS: ALOE VERA LEAF; DIMETHICONE; LEVANT COTTON SEED; CHAMOMILE; PROPANE; VINYL DIMETHICONE/METHICONE SILSESQUIOXANE CROSSPOLYMER; DISTEARDIMONIUM HECTORITE; GLYCERYL MONOSTEARATE; POLYGLYCERYL-3 DIISOSTEARATE; SILICA DIMETHYL SILYLATE; COCONUT; ALLANTOIN; BUTANE; ISOBUTANE; LECITHIN, SOYBEAN; WATER; GREEN TEA LEAF; CINNAMON BARK OIL; CYCLOMETHICONE 5; GLYCERIN; ISOPROPYL MYRISTATE; AVOCADO OIL; .ALPHA.-TOCOPHEROL ACETATE; ACORUS CALAMUS ROOT; ARGAN OIL; MACADAMIA OIL; SHEA BUTTER; PROPYLENE CARBONATE; MYRRH OIL

Antiperspirant Above Teen Dream Big Aerosol